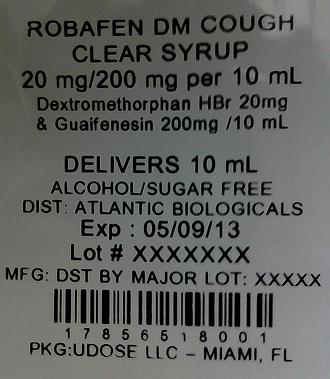 DRUG LABEL: Tussin Sugar Free Cough
                                    
NDC: 17856-5180 | Form: LIQUID
Manufacturer: Atlantic Biologicals Corps
Category: otc | Type: HUMAN OTC DRUG LABEL
Date: 20091114

ACTIVE INGREDIENTS: Dextromethorphan Hydrobromide 10 mg/5 mL; GUAIFENESIN 100 mg/5 mL
INACTIVE INGREDIENTS: acesulfame potassium; citric acid monohydrate; glycerin; methylparaben; polyethylene glycol; povidone; propylene glycol; saccharin sodium; sodium benzoate

Drug Facts

Active Ingredients

Dextromethorphan HBr,USP 10 mg Guaifenesin, USP 100 mg

Purpose

Dextromethorphan HBr...................Cough suppressant Guaifenesin, USP..............................Expectorant

Uses

• temporarily relieves cough due to minor throat and bronchial irritation as may occur with a cold • helps loosen phlegm (mucus) and thin bronchial secretions to make coughs more productive

Warnings

Do not use if you are now taking a prescription monoamine oxidase inhibitor (MAOI) (certain drugs for depression, psychiatric or emotional conditions, or Parkinson's disease), or for 2 weeks after stopping the MAOI drug. If you do not know if your prescription drug contains an MAOI, ask a doctor or pharmacist before taking this product.

Ask a Doctor before use if you have

• cough that occurs with too much phlegm (mucus) • cough that lasts or is chronic such as occurs with smoking, asthma, chronic bronchitis, or emphysema

When using this product

• do not use more than directed

Stop use and ask a doctor if

• cough lasts more than 7 days, comes back, or is accompanied by fever, rash, or persistent headache. These could be signs of a serious condition.

If pregnant or breast-feeding,

ask a health professional before use.

Keep this and all drugs out of the reach of children.

In case of accidental overdose, seek professional assistance or contact a Poison Control Center immediately.

Directions

• do not exceed 6 doses in a 24-hour period • this adult product is not intended for use in children under 12 years of age

adults and children 12 years and over 2 teaspoonfuls (tsps) every 4 hours children under 12 years do not use Age Dose

Other Information

sugar-free dosage cup provided

• store at controlled room temperature

alcohol-free

Inactive Ingredients

acesulfame potassium, citric acid, flavors, glycerin, methyl paraben, polyethylene glycol, povidone, propylene glycol, purified water, saccharin sodium, sodium benzoate